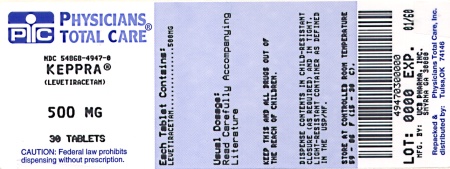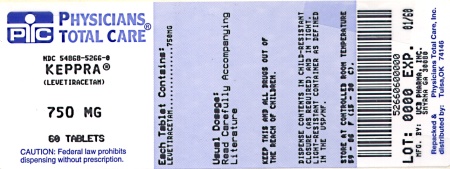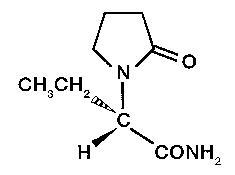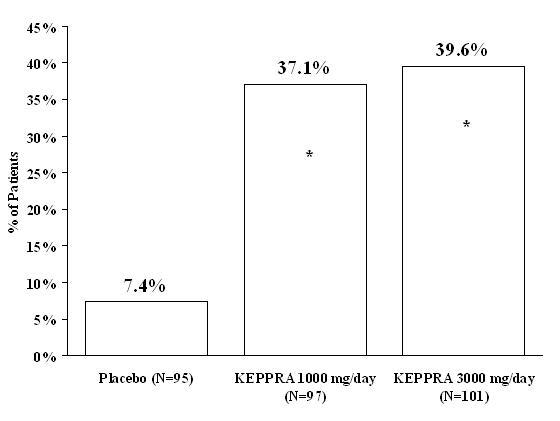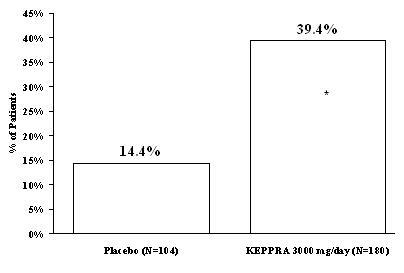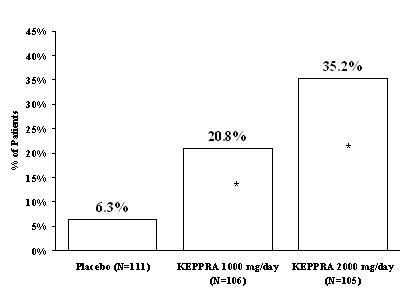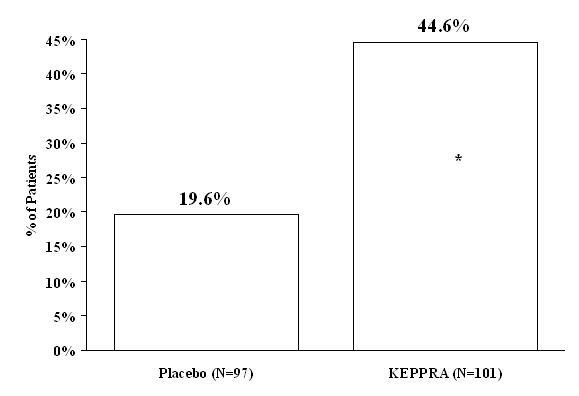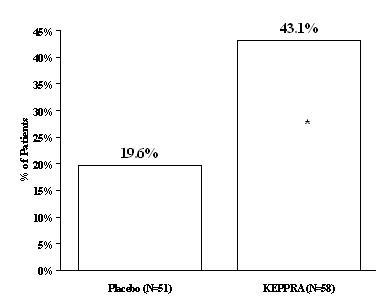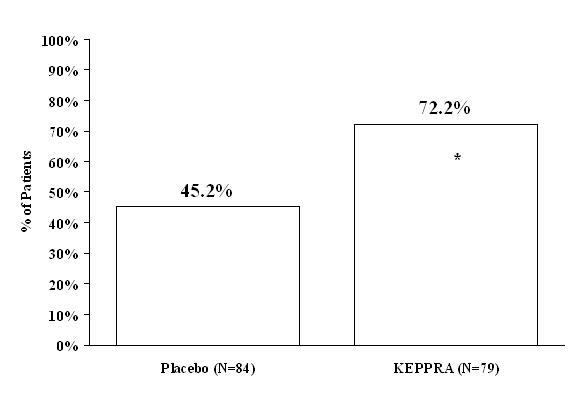 DRUG LABEL: Keppra
NDC: 54868-4947 | Form: TABLET, FILM COATED
Manufacturer: Physicians Total Care, Inc.
Category: prescription | Type: HUMAN PRESCRIPTION DRUG LABEL
Date: 20120607

ACTIVE INGREDIENTS: levetiracetam 500 mg/1 1
INACTIVE INGREDIENTS: silicon dioxide; croscarmellose sodium; magnesium stearate; POLYETHYLENE GLYCOL 3350; POLYETHYLENE GLYCOL 6000; polyvinyl alcohol; talc; titanium dioxide; ferric oxide yellow

HIGHLIGHTS OF PRESCRIBING INFORMATION

These highlights do not include all the information needed to use KEPPRA® safely and effectively. See full prescribing information for KEPPRA.
KEPPRA (levetiracetam) tablets, for oral use
KEPPRA (levetiracetam) oral solution
Initial U.S. Approval: 1999

RECENT MAJOR CHANGES

Indications and Usage, Partial Onset Seizures (1.1) | [12/2011]
Dosage and Administration, Partial Onset Seizures (2.1, 2.2, 2.5) | [12/2011]
Warnings and Precautions (5.1, 5.3, 5.4, 5.5, 5.7, 5.8, 5.9) | [12/2011]

1 INDICATIONS AND USAGE

KEPPRA is an antiepileptic drug indicated for adjunctive therapy in the treatment of:

- Partial onset seizures in patients one month of age and older with epilepsy (1.1)
- Myoclonic seizures in patients 12 years of age and older with juvenile myoclonic epilepsy (1.2)
- Primary generalized tonic-clonic seizures in patients 6 years of age and older with idiopathic generalized epilepsy (1.3)

2 DOSAGE AND ADMINISTRATION

- Use the oral solution for pediatric patients with body weight ≤ 20 kg (2.1).
- For pediatric patients, use weight-based dosing for the oral solution with a calibrated measuring device (not a household teaspoon or tablespoon) (2.1)

Partial Onset Seizures

- 1 Month To < 6 Months: 7 mg/kg twice daily, increase in increments of 7 mg/kg twice daily every 2 weeks to recommended dose of 21 mg/kg twice daily (2.2)
- 6 Months To < 4 Years: 10 mg/kg twice daily, increase in increments of 10 mg/kg twice daily every 2 weeks to recommended dose of 25 mg/kg twice daily (2.2)
- 4 Years To < 16 Years: 10 mg/kg twice daily, increase in increments of 10 mg/kg twice daily every 2 weeks to recommended dose of 30 mg/kg twice daily (2.2)
- Adults 16 Years And Older: 500 mg twice daily, increase as needed and tolerated in increments of 500 mg twice daily every 2 weeks to a maximum recommended dose of 1500 mg twice daily (2.2)

Myoclonic Seizures In Adults and Pediatric Patients 12 Years And Older

- 500 mg twice daily, increase by 500 mg twice daily every 2 weeks to recommended dose of 1500 mg twice daily (2.3)

Primary Generalized Tonic-Clonic Seizures

- 6 Years To < 16 Years: 10 mg/kg twice daily, increase in increments of 10 mg/kg twice daily every 2 weeks to recommended dose of 30 mg/kg twice daily (2.4)
- Adults 16 Years And Older: 500 mg twice daily, increase by 500 mg twice daily every 2 weeks to recommended dose of 1500 mg twice daily (2.4)

Adult patients with impaired renal function

- Dose adjustment is recommended, based on the patient's estimated creatinine clearance (2.5, 8.6)

3 DOSAGE FORMS AND STRENGTHS

- 250 mg, 500 mg, 750 mg, and 1000 mg film-coated, scored tablets (3)
- 100 mg/mL solution (3)

4 CONTRAINDICATIONS

- None (4)

5 WARNINGS AND PRECAUTIONS

- Psychiatric Symptoms: Behavioral abnormalities including psychotic symptoms, suicidal ideation, irritability, and aggressive behavior have been observed. Monitor patients for psychiatric signs and symptoms (5.1)
- Suicidal Behavior and Ideation: Monitor patients for new or worsening depression, suicidal thoughts/behavior, and/or unusual changes in mood or behavior (5.2)
- Somnolence and Fatigue: Monitor patients for these symptoms and advise patients not to drive or operate machinery until they have gained sufficient experience on KEPPRA (5.3)
- Withdrawal Seizures: KEPPRA must be gradually withdrawn (5.6)

6 ADVERSE REACTIONS

Most common adverse reactions (incidence in KEPPRA-treated patients is ≥ 5% more than in placebo-treated patients) include:

- Adult patients: somnolence, asthenia, infection and dizziness (6.1)
- Pediatric patients: fatigue, aggression, nasal congestion, decreased appetite, and irritability (6.1)

To report SUSPECTED ADVERSE REACTIONS, contact UCB, Inc. at 866-822-0068 or FDA at 1-800-FDA-1088 or www.fda.gov/medwatch.

8 USE IN SPECIFIC POPULATIONS

- Pregnancy: Plasma levels of levetiracetam may be decreased and therefore need to be monitored closely during pregnancy. Based on animal data, may cause fetal harm (5.9, 8.1)

FULL PRESCRIBING INFORMATION

1 INDICATIONS AND USAGE

1.1 Partial Onset Seizures

KEPPRA is indicated as adjunctive therapy in the treatment of partial onset seizures in adults and children 1 month of age and older with epilepsy.

1.2 Myoclonic Seizures In Patients With Juvenile Myoclonic Epilepsy

KEPPRA is indicated as adjunctive therapy in the treatment of myoclonic seizures in adults and adolescents 12 years of age and older with juvenile myoclonic epilepsy.

1.3 Primary Generalized Tonic-Clonic Seizures

KEPPRA is indicated as adjunctive therapy in the treatment of primary generalized tonic-clonic seizures in adults and children 6 years of age and older with idiopathic generalized epilepsy.

2 DOSAGE AND ADMINISTRATION

2.1 Important Administration Instructions

KEPPRA is given orally with or without food. The KEPPRA dosing regimen depends on the indication, age group, dosage form (tablets or oral solution), and renal function.

Prescribe the oral solution for pediatric patients with body weight ≤ 20 kg. Prescribe the oral solution or tablets for pediatric patients with body weight above 20 kg.

When using the oral solution, in pediatric patients, dosing is weight-based (mg per kg) using a calibrated measuring device (not a household teaspoon or tablespoon).

KEPPRA tablets should be swallowed whole. KEPPRA tablets should not be chewed or crushed.

2.2 Partial Onset Seizures

Adults 16 Years And Older

In clinical trials, daily doses of 1000 mg, 2000 mg, and 3000 mg, given as twice-daily dosing were shown to be effective. Although in some studies there was a tendency toward greater response with higher dose [see Clinical Studies (14.1)], a consistent increase in response with increased dose has not been shown.

Treatment should be initiated with a daily dose of 1000 mg/day, given as twice-daily dosing (500 mg twice daily). Additional dosing increments may be given (1000 mg/day additional every 2 weeks) to a maximum recommended daily dose of 3000 mg. Doses greater than 3000 mg/day have been used in open-label studies for periods of 6 months and longer. There is no evidence that doses greater than 3000 mg/day confer additional benefit.

Pediatric Patients

1 Month To < 6 Months

Treatment should be initiated with a daily dose of 14 mg/kg in 2 divided doses (7 mg/kg twice daily). The daily dose should be increased every 2 weeks by increments of 14 mg/kg to the recommended daily dose of 42 mg/kg (21 mg/kg twice daily). In the clinical trial, the mean daily dose was 35 mg/kg in this age group. The effectiveness of lower doses has not been studied.

6 Months To <4 Years:

Treatment should be initiated with a daily dose of 20 mg/kg in 2 divided doses (10 mg/kg twice daily). The daily dose should be increased in 2 weeks by an increment of 20 mg/kg to the recommended daily dose of 50 mg/kg (25 mg/kg twice daily). If a patient cannot tolerate a daily dose of 50 mg/kg, the daily dose may be reduced. In the clinical trial, the mean daily dose was 47 mg/kg in this age group.

4 Years To < 16 Years

Treatment should be initiated with a daily dose of 20 mg/kg in 2 divided doses (10 mg/kg twice daily). The daily dose should be increased every 2 weeks by increments of 20 mg/kg to the recommended daily dose of 60 mg/kg (30 mg/kg twice daily). If a patient cannot tolerate a daily dose of 60 mg/kg, the daily dose may be reduced. In the clinical efficacy trial, the mean daily dose was 44 mg/kg. The maximum daily dose was 3000 mg/day.

For KEPPRA tablet dosing in pediatric patients weighing 20 to 40 kg, treatment should be initiated with a daily dose of 500 mg given as twice daily dosing (250 mg twice daily). The daily dose should be increased every 2 weeks by increments of 500 mg to a maximum recommended daily dose of 1500 mg (750 mg twice daily).

For KEPPRA tablet dosing in pediatric patients weighing more than 40 kg, treatment should be initiated with a daily dose of 1000 mg/day given as twice daily dosing (500 mg twice daily). The daily dose should be increased every 2 weeks by increments of 1000 mg/day to a maximum recommended daily dose of 3000 mg (1500 mg twice daily).

KEPPRA Oral Solution Weight-Based Dosing Calculation For Pediatric Patients

The following calculation should be used to determine the appropriate daily dose of oral solution for pediatric patients:

Total daily dose (mL/day) = | Daily dose (mg/kg/day) × patient weight (kg)
Total daily dose (mL/day) = | -----------------------------------------
Total daily dose (mL/day) = | 100 mg/mL

2.3 Myoclonic Seizures In Patients 12 Years of Age and Older With Juvenile Myoclonic Epilepsy

Treatment should be initiated with a dose of 1000 mg/day, given as twice-daily dosing (500 mg twice daily). Dosage should be increased by 1000 mg/day every 2 weeks to the recommended daily dose of 3000 mg. The effectiveness of doses lower than 3000 mg/day has not been studied.

2.4 Primary Generalized Tonic-Clonic Seizures

Adults 16 Years And Older

Treatment should be initiated with a dose of 1000 mg/day, given as twice-daily dosing (500 mg twice daily). Dosage should be increased by 1000 mg/day every 2 weeks to the recommended daily dose of 3000 mg. The effectiveness of doses lower than 3000 mg/day has not been adequately studied.

Pediatric Patients Ages 6 To <16 Years

Treatment should be initiated with a daily dose of 20 mg/kg in 2 divided doses (10 mg/kg twice daily). The daily dose should be increased every 2 weeks by increments of 20 mg/kg to the recommended daily dose of 60 mg/kg (30 mg/kg twice daily). The effectiveness of doses lower than 60 mg/kg/day has not been adequately studied. Patients with body weight ≤20 kg should be dosed with oral solution. Patients with body weight above 20 kg can be dosed with either tablets or oral solution [see Dosage and Administration (2.1)]. Only whole tablets should be administered.

2.5 Adult Patients With Impaired Renal Function

KEPPRA dosing must be individualized according to the patient's renal function status. Recommended doses and adjustment for dose for adults are shown in Table 1. In order to calculate the dose recommended for patients with renal impairment, creatinine clearance adjusted for body surface area must be calculated. To do this an estimate of the patient's creatinine clearance (CLcr) in mL/min must first be calculated using the following formula:

CLcr= | [140-age (years)] × weight (kg)
CLcr= | ----------------------------------------- (× 0.85 for female patients)
CLcr= | 72 × serum creatinine (mg/dL)

Then CLcr is adjusted for body surface area (BSA) as follows:

CLcr (mL/min/1.73m^2)= | CLcr (mL/min)
CLcr (mL/min/1.73m^2)= | ---------------------------- × 1.73
CLcr (mL/min/1.73m^2)= | BSA subject (m^2)

Table 1: Dosing Adjustment Regimen For Adult Patients With Impaired Renal Function
Group | Creatinine Clearance (mL/min/1.73m^2) | Dosage (mg) | Frequency
Normal | > 80 | 500 to 1,500 | Every 12 hours
Mild | 50 – 80 | 500 to 1,000 | Every 12 hours
Moderate | 30 – 50 | 250 to 750 | Every 12 hours
Severe | < 30 | 250 to 500 | Every 12 hours
ESRD patients using dialysis | ---- | 500 to 1,000 [Following dialysis, a 250 to 500 mg supplemental dose is recommended.] | Every 24 hours

3 DOSAGE FORMS AND STRENGTHS

KEPPRA 250 mg tablets are blue, oblong-shaped, scored, film-coated, and debossed with "ucb 250" on one side.
KEPPRA 500 mg tablets are yellow, oblong-shaped, scored, film-coated, and debossed with "ucb 500" on one side.
KEPPRA 750 mg tablets are orange, oblong-shaped, scored, film-coated, and debossed with "ucb 750" on one side.
KEPPRA 1000 mg tablets are white, oblong-shaped, scored, film-coated, and debossed with "ucb 1000" on one side.
KEPPRA 100 mg/mL oral solution is a clear, colorless, grape-flavored liquid.

4 CONTRAINDICATIONS

None.

5 WARNINGS AND PRECAUTIONS

5.1 Psychiatric Reactions

In some patients KEPPRA causes behavioral abnormalities. The incidences of behavioral abnormalities in the myoclonic and primary generalized tonic-clonic seizure studies were comparable to those of the adult and pediatric partial onset seizure studies.

A total of 13.3% of adult KEPPRA-treated patients and 37.6% of pediatric KEPPRA-treated patients (4 to 16 years of age) compared to 6.2% and 18.6% of adult and pediatric placebo patients respectively, experienced non-psychotic behavioral symptoms (reported as aggression, agitation, anger, anxiety, apathy, depersonalization, depression, emotional lability, hostility, hyperkinesias, irritability, nervousness, neurosis, and personality disorder). A randomized double-blind, placebo-controlled study was performed to assess the neurocognitive and behavioral effects of KEPPRA as adjunctive therapy in pediatric patients (4 to 16 years of age). The results from an exploratory analysis indicated a worsening in KEPPRA-treated patients on aggressive behavior (one of eight behavior dimensions) as measured in a standardized and systematic way using a validated instrument, the Achenbach Child Behavior Checklist (CBCL/6-18).

In pediatric patients 1 month to < 4 years of age, irritability was reported in 11.7% of the KEPPRA-treated patients compared to 0% of placebo patients.

A total of 1.7% of adult KEPPRA-treated patients discontinued treatment due to behavioral adverse events, compared to 0.2% of placebo patients. The treatment dose was reduced in 0.8% of adult KEPPRA-treated patients and in 0.5% of placebo patients. Overall, 10.9% of KEPPRA-treated pediatric patients experienced behavioral symptoms associated with discontinuation or dose reduction, compared to 6.2% of placebo patients.

One percent of adult KEPPRA-treated patients, 2% of children 4 to 16 years of age, and 17% of children 1 month to <4 years of age experienced psychotic symptoms, compared to 0.2%, 2%, and 5% respectively, in the placebo patients. In the controlled study that assessed the neurocognitive and behavioral effects of KEPPRA in pediatric patients 4 to 16 years of age, 1 (1.6%) KEPPRA-treated patient experienced paranoia compared to no placebo patients. There were 2 (3.1%) KEPPRA-treated patients that experienced confusional state compared to no placebo patients [see Use in Specific Populations (8.4)].

Two (0.3%) adult KEPPRA-treated patients were hospitalized and their treatment was discontinued due to psychosis. Both events, reported as psychosis, developed within the first week of treatment and resolved within 1 to 2 weeks following treatment discontinuation. There was no difference between drug and placebo-treated patients in the incidence of the pediatric patients who discontinued treatment due to psychotic and non-psychotic adverse reactions.

The above psychiatric signs symptoms should be monitored.

5.2 Suicidal Behavior and Ideation

Antiepileptic drugs (AEDs), including KEPPRA, increase the risk of suicidal thoughts or behavior in patients taking these drugs for any indication. Patients treated with any AED for any indication should be monitored for the emergence or worsening of depression, suicidal thoughts or behavior, and/or any unusual changes in mood or behavior.

Pooled analyses of 199 placebo-controlled clinical trials (mono- and adjunctive therapy) of 11 different AEDs showed that patients randomized to one of the AEDs had approximately twice the risk (adjusted Relative Risk 1.8, 95% CI:1.2, 2.7) of suicidal thinking or behavior compared to patients randomized to placebo. In these trials, which had a median treatment duration of 12 weeks, the estimated incidence rate of suicidal behavior or ideation among 27,863 AED-treated patients was 0.43%, compared to 0.24% among 16,029 placebo-treated patients, representing an increase of approximately one case of suicidal thinking or behavior for every 530 patients treated. There were four suicides in drug-treated patients in the trials and none in placebo-treated patients, but the number is too small to allow any conclusion about drug effect on suicide.

The increased risk of suicidal thoughts or behavior with AEDs was observed as early as one week after starting drug treatment with AEDs and persisted for the duration of treatment assessed. Because most trials included in the analysis did not extend beyond 24 weeks, the risk of suicidal thoughts or behavior beyond 24 weeks could not be assessed.

The risk of suicidal thoughts or behavior was generally consistent among drugs in the data analyzed. The finding of increased risk with AEDs of varying mechanisms of action and across a range of indications suggests that the risk applies to all AEDs used for any indication. The risk did not vary substantially by age (5-100 years) in the clinical trials analyzed. Table 2 shows absolute and relative risk by indication for all evaluated AEDs.

Table 2 | Risk by indication for antiepileptic drugs in the pooled analysis
Indication | Placebo Patients with Events Per 1000 Patients | Drug Patients with Events Per 1000 Patients | Relative Risk: Incidence of Events in Drug Patients/Incidence in Placebo Patients | Risk Difference: Additional Drug Patients with Events Per 1000 Patients
Epilepsy | 1.0 | 3.4 | 3.5 | 2.4
Psychiatric | 5.7 | 8.5 | 1.5 | 2.9
Other | 1.0 | 1.8 | 1.9 | 0.9
Total | 2.4 | 4.3 | 1.8 | 1.9

The relative risk for suicidal thoughts or behavior was higher in clinical trials for epilepsy than in clinical trials for psychiatric or other conditions, but the absolute risk differences were similar for the epilepsy and psychiatric indications.

Anyone considering prescribing KEPPRA or any other AED must balance the risk of suicidal thoughts or behaviors with the risk of untreated illness. Epilepsy and many other illnesses for which AEDs are prescribed are themselves associated with morbidity and mortality and an increased risk of suicidal thoughts and behavior. Should suicidal thoughts and behavior emerge during treatment, the prescriber needs to consider whether the emergence of these symptoms in any given patient may be related to the illness being treated.

Patients, their caregivers, and families should be informed that AEDs increase the risk of suicidal thoughts and behavior and should be advised of the need to be alert for the emergence or worsening of the signs and symptoms of depression, any unusual changes in mood or behavior, or the emergence of suicidal thoughts, behavior, or thoughts about self-harm. Behaviors of concern should be reported immediately to healthcare providers.

5.3 Somnolence and Fatigue

In some patients, KEPPRA causes somnolence and fatigue. The incidences of somnolence and fatigue provided below are from controlled adult partial onset seizure studies. In general, the incidences of somnolence and fatigue in the pediatric partial onset seizure studies, and in pediatric and adult myoclonic and primary generalized tonic-clonic seizure studies were comparable to those of the adult partial onset seizure studies.

In controlled trials of adult patients with epilepsy experiencing partial onset seizures, 14.8% of KEPPRA-treated patients reported somnolence, compared to 8.4% of placebo patients. There was no clear dose response up to 3000 mg/day. In a study where there was no titration, about 45% of patients receiving 4000 mg/day reported somnolence. The somnolence was considered serious in 0.3% of the treated patients, compared to 0% in the placebo group. About 3% of KEPPRA-treated patients discontinued treatment due to somnolence, compared to 0.7% of placebo patients. In 1.4% of treated patients and in 0.9% of placebo patients the dose was reduced, while 0.3% of the treated patients were hospitalized due to somnolence.

In controlled trials of adult patients with epilepsy experiencing partial onset seizures, 14.7% of KEPPRA-treated patients reported asthenia, compared to 9.1% of placebo patients. Treatment was discontinued due to asthenia in 0.8% of treated patients as compared to 0.5% of placebo patients. In 0.5% of treated patients and in 0.2% of placebo patients the dose was reduced due to asthenia.

Somnolence and asthenia occurred most frequently within the first 4 weeks of treatment.

Patients should be monitored for these signs and symptoms and advised not to drive or operate machinery until they have gained sufficient experience on KEPPRA to gauge whether it adversely affects their ability to drive or operate machinery.

5.4 Serious Dermatological Reactions

Serious dermatological reactions, including Stevens-Johnson syndrome (SJS) and toxic epidermal necrolysis (TEN), have been reported in both children and adults treated with levetiracetam. The median time of onset is reported to be 14 to 17 days, but cases have been reported at least four months after initiation of treatment. Recurrence of the serious skin reactions following rechallenge with levetiracetam has also been reported. Keppra should be discontinued at the first sign of a rash, unless the rash is clearly not drug-related. If signs or symptoms suggest SJS/TEN, use of this drug should not be resumed and alternative therapy should be considered.

5.5 Coordination Difficulties

Coordination difficulties were only observed in the adult partial onset seizure studies. A total of 3.4% of adult KEPPRA-treated patients experienced coordination difficulties, (reported as either ataxia, abnormal gait, or incoordination) compared to 1.6% of placebo patients. A total of 0.4% of patients in controlled trials discontinued KEPPRA treatment due to ataxia, compared to 0% of placebo patients. In 0.7% of treated patients and in 0.2% of placebo patients the dose was reduced due to coordination difficulties, while one of the treated patients was hospitalized due to worsening of pre-existing ataxia. These events occurred most frequently within the first 4 weeks of treatment.

Patients should be monitored for these signs and symptoms and advised not to drive or operate machinery until they have gained sufficient experience on KEPPRA to gauge whether it could adversely affect their ability to drive or operate machinery.

5.6 Withdrawal Seizures

Antiepileptic drugs, including KEPPRA, should be withdrawn gradually to minimize the potential of increased seizure frequency.

5.7 Hematologic Abnormalities

Partial Onset Seizures

Adults

Minor, but statistically significant, decreases compared to placebo in total mean RBC count (0.03 x 10^6/mm^3), mean hemoglobin (0.09 g/dL), and mean hematocrit (0.38%), were seen in KEPPRA-treated patients in controlled trials.

A total of 3.2% of treated and 1.8% of placebo patients had at least one possibly significant (≤2.8 × 10^9/L) decreased WBC, and 2.4% of treated and 1.4% of placebo patients had at least one possibly significant (≤1.0 × 10^9/L) decreased neutrophil count. Of the treated patients with a low neutrophil count, all but one rose towards or to baseline with continued treatment. No patient was discontinued secondary to low neutrophil counts.

Pediatric Patients 4 Years To < 16 Years

Statistically significant decreases in WBC and neutrophil counts were seen in KEPPRA-treated patients as compared to placebo. The mean decreases from baseline in the KEPPRA-treated group were -0.4 × 10^9/L and -0.3 × 10^9/L, respectively, whereas there were small increases in the placebo group. Mean relative lymphocyte counts increased by 1.7% in KEPPRA-treated patients, compared to a decrease of 4% in placebo patients (statistically significant).

In the controlled trial, more KEPPRA-treated patients had a possibly clinically significant abnormally low WBC value (3.0% KEPPRA-treated versus 0% placebo), however, there was no apparent difference between treatment groups with respect to neutrophil count (5.0% KEPPRA-treated versus 4.2% placebo). No patient was discontinued secondary to low WBC or neutrophil counts.

In the controlled cognitive and neuropsychological safety study, two subjects (6.1%) in the placebo group and 5 subjects (8.6%) in the KEPPRA-treated group had high eosinophil count values that were possibly clinically significant (≥10% or ≥0.7×10^9/L).

Juvenile Myoclonic Epilepsy

Although there were no obvious hematologic abnormalities observed in patients with JME, the limited number of patients makes any conclusion tentative. The data from the partial seizure patients should be considered to be relevant for JME patients.

5.8 Blood Pressure Increases

In a randomized, placebo-controlled study in patients aged 1 month to <4 years of age, a significantly higher risk of at least one measured increase in diastolic blood pressure was observed in the KEPPRA-treated patients (17%) compared to the placebo-treated patients (2%). There was no overall difference in mean diastolic blood pressure between the treatment groups. This disparity between the KEPPRA and placebo treatment groups was not observed in the studies of older children or in adults.

5.9 Seizure Control During Pregnancy

Physiological changes may gradually decrease plasma levels of levetiracetam throughout pregnancy. This decrease is more pronounced during the third trimester. It is recommended that patients be monitored carefully during pregnancy. Close monitoring should continue through the postpartum period especially if the dose was changed during pregnancy.

6 ADVERSE REACTIONS

The following adverse reactions are discussed in more details in other sections of labeling:

- Psychiatric Symptoms [see Warnings and Precautions (5.1)]
- Suicidal Behavior and Ideation [see Warnings and Precautions (5.2)]
- Somnolence and Fatigue [see Warnings and Precautions (5.3)]
- Serious Dermatological Reactions [see Warnings and Precautions (5.4)]
- Coordination Difficulties [see Warnings and Precautions (5.5)]
- Withdrawal Seizures [see Warnings and Precautions (5.6)]
- Hematologic Abnormalities [see Warnings and Precautions (5.7)]
- Blood Pressure Increases [see Warnings and Precautions (5.8)]
- Seizure Control During Pregnancy [see Warnings and Precautions (5.9)]

6.1 Clinical Trials Experience

Because clinical trials are conducted under widely varying conditions, adverse reaction rates observed in the clinical trials of a drug cannot be directly compared to rates in the clinical trials of another drug and may not reflect the rates observed in practice.

The prescriber should be aware that the adverse reaction incidence figures in the following tables, obtained when KEPPRA was added to concurrent AED therapy, cannot be used to predict the frequency of adverse reactions in the course of usual medical practice where patient characteristics and other factors may differ from those prevailing during clinical trials. Similarly, the cited frequencies cannot be directly compared with figures obtained from other clinical investigations involving different treatments, uses, or investigators. An inspection of these frequencies, however, does provide the prescriber with one basis to estimate the relative contribution of drug and non-drug factors to the adverse reaction incidences in the population studied.

Partial Onset Seizures

Adults

In controlled clinical studies in adults with partial onset seizures, the most frequently reported adverse reactions in patients receiving KEPPRA in combination with other AEDs were somnolence, asthenia, infection and dizziness. Of the most frequently reported adverse reactions in adults experiencing partial onset seizures, asthenia, somnolence and dizziness appeared to occur predominantly during the first 4 weeks of treatment with KEPPRA.

Table 3 lists adverse reactions that occurred in at least 1% of adult epilepsy patients treated with KEPPRA participating in placebo-controlled studies and were numerically more common than in patients treated with placebo. In these studies, either KEPPRA or placebo was added to concurrent AED therapy. Adverse reactions were usually mild to moderate in intensity.

Table 3: Incidence (%) Of Adverse Reactions In Placebo-Controlled, Add-On Studies In Adults Experiencing Partial Onset Seizures By Body System (Adverse Reactions Occurred In At Least 1% Of KEPPRA-Treated Patients And Occurred More Frequently Than Placebo-Treated Patients)
Body System/ Adverse Reaction | KEPPRA (N=769) % | Placebo (N=439) %
Body as a Whole
Asthenia | 15 | 9
Headache | 14 | 13
Infection | 13 | 8
Pain | 7 | 6
Digestive System
Anorexia | 3 | 2
Nervous System
Somnolence | 15 | 8
Dizziness | 9 | 4
Depression | 4 | 2
Nervousness | 4 | 2
Ataxia | 3 | 1
Vertigo | 3 | 1
Amnesia | 2 | 1
Anxiety | 2 | 1
Hostility | 2 | 1
Paresthesia | 2 | 1
Emotional Lability | 2 | 0
Respiratory System
Pharyngitis | 6 | 4
Rhinitis | 4 | 3
Cough Increased | 2 | 1
Sinusitis | 2 | 1
Special Senses
Diplopia | 2 | 1

In controlled adult clinical studies, 15% of patients receiving KEPPRA and 12% receiving placebo either discontinued or had a dose reduction as a result of an adverse event. Table 4 lists the most common (>1%) adverse reactions that resulted in discontinuation or dose reduction and that occurred more frequently in KEPPRA-treated patients than in placebo-treated patients.

Table 4: Adverse Reactions That Most Commonly Resulted In Discontinuation Or Dose Reduction That Occurred More Frequently In KEPPRA-Treated Patients In Placebo-Controlled Studies In Adult Patients Experiencing Partial Onset Seizures
Adverse Reaction | KEPPRA (N=769) % | Placebo (N=439) %
Dizziness | 1 | 0
Somnolence | 4 | 2

Pediatric Patients 4 Years To <16 Years

The adverse reaction data presented below was obtained from a pooled analysis of two controlled pediatric clinical studies in children 4 to 16 years of age with partial onset seizures. The adverse reactions most frequently reported with the use of KEPPRA in combination with other AEDs, not seen at an equivalent frequency among placebo-treated patients, were fatigue, aggression, nasal congestion, decreased appetite, and irritability.

Table 5 lists adverse reactions from the pooled pediatric controlled studies (4 to 16 years of age) that occurred in at least 2% of pediatric KEPPRA-treated patients and were numerically more common than in pediatric patients treated with placebo. In these studies, either KEPPRA or placebo was added to concurrent AED therapy. Adverse reactions were usually mild to moderate in intensity.

Table 5: Incidence (%) Of Adverse Reactions In Pooled Placebo-Controlled, Add-On Studies In Pediatric Patients Ages 4 to 16 Years Experiencing Partial Onset Seizures By Body System (Adverse Reactions Occurred In At Least 2% Of KEPPRA-Treated Patients And Occurred More Frequently Than Placebo-Treated Patients)
Body System/ Adverse Reaction | KEPPRA (N=165) % | Placebo (N=131) %
Ear and Labyrinth Disorders
Ear Pain | 2 | 1
Eye Disorders
Conjunctivitis | 2 | 0
Gastrointestinal Disorders
Vomiting | 15 | 12
Abdominal Pain Upper | 9 | 8
Diarrhea | 6 | 5
Constipation | 3 | 1
General Disorders and Administration Site Conditions
Fatigue | 11 | 5
Infections and Infestations
Nasopharyngitis | 15 | 12
Influenza | 3 | 1
Gastroenteritis | 2 | 0
Rhinitis | 2 | 0
Injury, Poisoning and Procedural Complications
Head Injury | 4 | 0
Contusion | 3 | 1
Fall | 3 | 2
Joint Sprain | 2 | 1
Metabolism and Nutrition Disorders
Decreased Appetite | 8 | 2
Anorexia | 4 | 3
Musculoskeletal and Connective Tissue Disorders
Arthralgia | 2 | 0
Neck Pain | 2 | 1
Nervous System
Headache | 19 | 15
Somnolence | 13 | 9
Dizziness | 7 | 5
Lethargy | 6 | 2
Sedation | 2 | 1
Psychiatric Disorders
Aggression | 10 | 5
Abnormal Behavior | 7 | 4
Irritability | 7 | 1
Insomnia | 5 | 3
Agitation | 4 | 1
Depression | 3 | 1
Mood Altered | 3 | 1
Affect Lability | 2 | 1
Anxiety | 2 | 1
Confusional State | 2 | 0
Mood Swings | 2 | 1
Respiratory, Thoracic and Mediastinal Disorders
Cough | 9 | 5
Nasal Congestion | 9 | 2
Pharyngolaryngeal Pain | 7 | 4

In the well controlled pooled pediatric clinical studies in patients 4-16 years of age, 7% of patients receiving KEPPRA and 9% receiving placebo discontinued as a result of an adverse event.

Pediatric Patients 1 Month To < 4 Years

In the 7-day, controlled pediatric clinical study in children 1 month to less than 4 years of age with partial onset seizures, the adverse reactions most frequently reported with the use of KEPPRA in combination with other AEDs, not seen at an equivalent frequency among placebo-treated patients, were somnolence and irritability. Because of the shorter exposure period, incidences of adverse reactions are expected to be lower then in other pediatric studies in older patients. Therefore, other controlled pediatric data, presented above, should also be considered to apply to this age group.

Table 6 lists adverse reactions that occurred in at least 5% of pediatric epilepsy patients (ages 1 month to < 4 years) treated with KEPPRA participating in the placebo-controlled study and were numerically more common than in patients treated with placebo. In this study, either KEPPRA or placebo was added to concurrent AED therapy. Adverse reactions were usually mild to moderate in intensity.

Table 6: Incidence (%) Of Adverse Reactions In A Placebo-Controlled, Add-On Study In Pediatric Patients Ages 1 Month to < 4 Years Experiencing Partial Onset Seizures By Body System (Adverse Reactions Occurred In At Least 5% Of KEPPRA-Treated Patients And Occurred More Frequently Than Placebo-Treated Patients)
Body System/ Adverse Reaction | KEPPRA (N=60) % | Placebo (N=56) %
Nervous System
Somnolence | 13 | 2
Psychiatric Disorders
Irritability | 12 | 0

In the 7-day controlled pediatric clinical study in patients 1 month to < 4 years of age, 3% of patients receiving KEPPRA and 2% receiving placebo either discontinued or had a dose reduction as a result of an adverse event. There was no adverse event that resulted in discontinuation for more than one patient.

Myoclonic Seizures

Although the pattern of adverse reactions in this study seems somewhat different from that seen in patients with partial seizures, this is likely due to the much smaller number of patients in this study compared to partial seizure studies. The adverse reaction pattern for patients with JME is expected to be essentially the same as for patients with partial seizures.

In the well-controlled clinical study that included both adolescent (12 to 16 years of age) and adult patients with myoclonic seizures, the most frequently reported adverse reactions in patients using KEPPRA in combination with other AEDs, not seen at an equivalent frequency among placebo-treated patients, were somnolence, neck pain, and pharyngitis.

Table 7 lists adverse reactions that occurred in at least 5% of juvenile myoclonic epilepsy patients experiencing myoclonic seizures treated with KEPPRA and were numerically more common than in patients treated with placebo. In this study, either KEPPRA or placebo was added to concurrent AED therapy. Adverse reactions were usually mild to moderate in intensity.

Table 7: Incidence (%) Of Adverse Reactions In A Placebo-Controlled, Add-On Study In Patients 12 Years Of Age And Older With Myoclonic Seizures By Body System (Adverse Reactions Occurred In At Least 5% Of KEPPRA-Treated Patients And Occurred More Frequently Than Placebo-Treated Patients)
Body System/ Adverse Reaction | KEPPRA (N=60) % | Placebo (N=60) %
Ear and labyrinth disorders
Vertigo | 5 | 3
Infections and infestations
Pharyngitis | 7 | 0
Influenza | 5 | 2
Musculoskeletal and connective tissue disorders
Neck pain | 8 | 2
Nervous system disorders
Somnolence | 12 | 2
Psychiatric disorders
Depression | 5 | 2

In the placebo-controlled study, 8% of patients receiving KEPPRA and 2% receiving placebo either discontinued or had a dose reduction as a result of an adverse reaction. The adverse reactions that led to discontinuation or dose reduction in the well-controlled study and occurred more frequently in KEPPRA-treated patients than in placebo-treated patients are presented in Table 8.

Table 8: Adverse Reactions That Resulted In Discontinuation Or Dose Reduction That Occurred More Frequently in KEPPRA-Treated Patients In The Placebo-Controlled Study In Patients With Juvenile Myoclonic Epilepsy
Adverse Reaction | KEPPRA (N=60) % | Placebo (N=60) %
Anxiety | 3 | 2
Depressed mood | 2 | 0
Depression | 2 | 0
Diplopia | 2 | 0
Hypersomnia | 2 | 0
Insomnia | 2 | 0
Irritability | 2 | 0
Nervousness | 2 | 0
Somnolence | 2 | 0

Primary Generalized Tonic-Clonic Seizures

Although the pattern of adverse reactions in this study seems somewhat different from that seen in patients with partial seizures, this is likely due to the much smaller number of patients in this study compared to partial seizure studies. The adverse reaction pattern for patients with PGTC seizures is expected to be essentially the same as for patients with partial seizures.

In the well-controlled clinical study that included patients 4 years of age and older with primary generalized tonic-clonic (PGTC) seizures, the most frequently reported adverse reaction in patients using KEPPRA in combination with other AEDs, not seen at an equivalent frequency among placebo-treated patients, was nasopharyngitis.

Table 9 lists adverse reactions that occurred in at least 5% of idiopathic generalized epilepsy patients experiencing PGTC seizures treated with KEPPRA and were numerically more common than in patients treated with placebo. In this study, either KEPPRA or placebo was added to concurrent AED therapy. Adverse reactions were usually mild to moderate in intensity.

Table 9: Incidence (%) Of Adverse Reactions In A Placebo-Controlled, Add-On Study In Patients 4 Years Of Age And Older With PGTC Seizures By MedDRA System Organ Class (Adverse Reactions Occurred In At Least 5% Of KEPPRA-Treated Patients And Occurred More Frequently Than Placebo-Treated Patients)
Body System/ Adverse Reaction | KEPPRA (N=79) % | Placebo (N=84) %
Gastrointestinal disorders
Diarrhea | 8 | 7
General disorders and administration site conditions
Fatigue | 10 | 8
Infections and infestations
Nasopharyngitis | 14 | 5
Psychiatric disorders
Irritability | 6 | 2
Mood Swings | 5 | 1

In the placebo-controlled study, 5% of patients receiving KEPPRA and 8% receiving placebo either discontinued or had a dose reduction during the treatment period as a result of an adverse reaction.

This study was too small to adequately characterize the adverse reactions that could be expected to result in discontinuation of treatment in this population. It is expected that the adverse reactions that would lead to discontinuation in this population would be similar to those resulting in discontinuation in other epilepsy trials (see tables 4 and 8).

In addition, the following adverse reactions were seen in other well-controlled adult studies of KEPPRA: balance disorder, disturbance in attention, eczema, memory impairment, myalgia, and vision blurred.

Comparison Of Gender, Age And Race

The overall adverse reaction profile of KEPPRA was similar between females and males. There are insufficient data to support a statement regarding the distribution of adverse experience reports by age and race.

6.2 Postmarketing Experience

The following adverse reactions have been identified during postapproval use of KEPPRA. Because these reactions are reported voluntarily from a population of uncertain size, it is not always possible to reliably estimate their frequency or establish a causal relationship to drug exposure.

In addition to the adverse reactions listed above, [see Adverse Reactions (6.1)], the following adverse events have been reported in patients receiving marketed KEPPRA worldwide. The listing is alphabetized: abnormal liver function test, choreoathetosis, dyskinesia, erythema multiforme, hepatic failure, hepatitis, leukopenia, neutropenia, pancreatitis, pancytopenia (with bone marrow suppression identified in some of these cases), thrombocytopenia, and weight loss. Alopecia has been reported with KEPPRA use; recovery was observed in majority of cases where KEPPRA was discontinued.

7 DRUG INTERACTIONS

No significant pharmacokinetic interactions were observed between levetiracetam or its major metabolite and concomitant medications via human liver cytochrome P450 isoforms, epoxide hydrolase, UDP-glucuronidation enzymes, P-glycoprotein, or renal tubular secretion [see Clinical Pharmacology (12.3)].

8 USE IN SPECIFIC POPULATIONS

8.1 Pregnancy

Keppra levels may decrease during pregnancy [see Warnings and Precautions (5.9)].

Pregnancy Category C

There are no adequate and well-controlled studies in pregnant women. In animal studies, levetiracetam produced evidence of developmental toxicity, including teratogenic effects, at doses similar to or greater than human therapeutic doses. KEPPRA should be used during pregnancy only if the potential benefit justifies the potential risk to the fetus.

Oral administration of levetiracetam to female rats throughout pregnancy and lactation led to increased incidences of minor fetal skeletal abnormalities and retarded offspring growth pre- and/or postnatally at doses ≥350 mg/kg/day (equivalent to the maximum recommended human dose of 3000 mg [MRHD] on a mg/m^2 basis) and with increased pup mortality and offspring behavioral alterations at a dose of 1800 mg/kg/day (6 times the MRHD on a mg/m^2 basis). The developmental no effect dose was 70 mg/kg/day (0.2 times the MRHD on a mg/m^2 basis). There was no overt maternal toxicity at the doses used in this study.

Oral administration of levetiracetam to pregnant rabbits during the period of organogenesis resulted in increased embryofetal mortality and increased incidences of minor fetal skeletal abnormalities at doses ≥600 mg/kg/day (4 times MRHD on a mg/m^2 basis) and in decreased fetal weights and increased incidences of fetal malformations at a dose of 1800 mg/kg/day (12 times the MRHD on a mg/m^2 basis). The developmental no effect dose was 200 mg/kg/day (equivalent to the MRHD on a mg/m^2 basis). Maternal toxicity was also observed at 1800 mg/kg/day.

When levetiracetam was administered orally to pregnant rats during the period of organogenesis, fetal weights were decreased and the incidence of fetal skeletal variations was increased at a dose of 3600 mg/kg/day (12 times the MRHD). 1200 mg/kg/day (4 times the MRHD) was a developmental no effect dose. There was no evidence of maternal toxicity in this study.

Treatment of rats with levetiracetam during the last third of gestation and throughout lactation produced no adverse developmental or maternal effects at doses of up to 1800 mg/kg/day (6 times the MRHD on a mg/m^2 basis).

Pregnancy Registries

To provide information regarding the effects of in utero exposure to KEPPRA, physicians are advised to recommend that pregnant patients taking KEPPRA enroll in the North American Antiepileptic Drug (NAAED) pregnancy registry. This can be done by calling the toll free number 1-888-233-2334, and must be done by the patients themselves. Information on the registry can also be found at the website http://www.aedpregnancyregistry.org/.

UCB, Inc. has established the UCB AED Pregnancy Registry to advance scientific knowledge about safety and outcomes associated with pregnant women being treated with all UCB antiepileptic drugs, including KEPPRA. To ensure broad program access and reach, either a healthcare provider or the patient can initiate enrollment in the UCB AED Pregnancy Registry by calling 1-888-537-7734 (toll free).

8.2 Labor And Delivery

The effect of KEPPRA on labor and delivery in humans is unknown.

8.3 Nursing Mothers

Levetiracetam is excreted in human milk. Because of the potential for serious adverse reactions in nursing infants from KEPPRA, a decision should be made whether to discontinue nursing or discontinue the drug, taking into account the importance of the drug to the mother.

8.4 Pediatric Use

The safety and effectiveness of KEPPRA in the adjunctive treatment of partial onset seizures in pediatric patients age 1 month to 16 years old with epilepsy have been established [see Clinical Studies (14.1)]. The dosing recommendation in these pediatric patients varies according to age group and is weight-based [see Dosage and Administration (2.2)].

The safety and effectiveness of KEPPRA as adjunctive treatment of myoclonic seizures in adolescents 12 years of age and older with juvenile myoclonic epilepsy have been established [see Clinical Studies (14.2)].

The safety and effectiveness of KEPPRA as adjunctive therapy in the treatment of primary generalized tonic-clonic seizures in pediatric patients 6 years of age and older with idiopathic generalized epilepsy have been established [see Clinical Studies (14.3)].

A 3-month, randomized, double-blind, placebo-controlled study was performed to assess the neurocognitive and behavioral effects of KEPPRA as adjunctive therapy in 98 (KEPPRA N=64, placebo N=34) pediatric patients, ages 4 to 16 years old, with partial seizures that were inadequately controlled. The target dose was 60 mg/kg/day. Neurocognitive effects were measured by the Leiter-R Attention and Memory (AM) Battery, which measures various aspects of a child's memory and attention. Although no substantive differences were observed between the placebo and drug treated groups in the median change from baseline in this battery, the study was not adequate to assess formal statistical non-inferiority of the drug and placebo. The Achenbach Child Behavior Checklist (CBCL/6-18), a standardized validated tool used to assess a child's competencies and behavioral/emotional problems, was also assessed in this study. An analysis of the CBCL/6-18 indicated on average a worsening in KEPPRA-treated patients in aggressive behavior, one of the eight syndrome scores [see Warnings and Precautions (5.1)].

Studies of levetiracetam in juvenile rats (dosing from day 4 through day 52 of age) and dogs (dosing from week 3 through week 7 of age) at doses of up to 1800 mg/kg/day (approximately 7 and 24 times, respectively, the maximum recommended pediatric dose of 60 mg/kg/day on a mg/m^2 basis) did not indicate a potential for age-specific toxicity.

8.5 Geriatric Use

There were 347 subjects in clinical studies of levetiracetam that were 65 and over. No overall differences in safety were observed between these subjects and younger subjects. There were insufficient numbers of elderly subjects in controlled trials of epilepsy to adequately assess the effectiveness of KEPPRA in these patients. Levetiracetam is known to be substantially excreted by the kidney, and the risk of adverse reactions to this drug may be greater in patients with impaired renal function. Because elderly patients are more likely to have decreased renal function, care should be taken in dose selection, and it may be useful to monitor renal function [see Clinical Pharmacology (12.3)].

8.6 Use In Patients With Impaired Renal Function

Clearance of levetiracetam is decreased in patients with renal impairment and is correlated with creatinine clearance [see Clinical Pharmacology (12.3)]. Dose adjustment is recommended for patients with impaired renal function and supplemental doses should be given to patients after dialysis [see Dosage and Administration (2.5)].

10 OVERDOSAGE

10.1 Signs, Symptoms And Laboratory Findings Of Acute Overdosage In Humans

The highest known dose of KEPPRA received in the clinical development program was 6000 mg/day. Other than drowsiness, there were no adverse events in the few known cases of overdose in clinical trials. Cases of somnolence, agitation, aggression, depressed level of consciousness, respiratory depression and coma were observed with KEPPRA overdoses in postmarketing use.

10.2 Management Of Overdose

There is no specific antidote for overdose with KEPPRA. If indicated, elimination of unabsorbed drug should be attempted by emesis or gastric lavage; usual precautions should be observed to maintain airway. General supportive care of the patient is indicated including monitoring of vital signs and observation of the patient's clinical status. A Certified Poison Control Center should be contacted for up to date information on the management of overdose with KEPPRA.

10.3 Hemodialysis

Standard hemodialysis procedures result in significant clearance of levetiracetam (approximately 50% in 4 hours) and should be considered in cases of overdose. Although hemodialysis has not been performed in the few known cases of overdose, it may be indicated by the patient's clinical state or in patients with significant renal impairment.

11 DESCRIPTION

KEPPRA is an antiepileptic drug available as 250 mg (blue), 500 mg (yellow), 750 mg (orange), and 1000 mg (white) tablets and as a clear, colorless, grape-flavored liquid (100 mg/mL) for oral administration.

The chemical name of levetiracetam, a single enantiomer, is (-)-(S)-α-ethyl-2-oxo-1-pyrrolidine acetamide, its molecular formula is C8H14N2O2 and its molecular weight is 170.21. Levetiracetam is chemically unrelated to existing antiepileptic drugs (AEDs). It has the following structural formula:

Levetiracetam is a white to off-white crystalline powder with a faint odor and a bitter taste. It is very soluble in water (104.0 g/100 mL). It is freely soluble in chloroform (65.3 g/100 mL) and in methanol (53.6 g/100 mL), soluble in ethanol (16.5 g/100 mL), sparingly soluble in acetonitrile (5.7 g/100 mL) and practically insoluble in n-hexane. (Solubility limits are expressed as g/100 mL solvent.)

KEPPRA tablets contain the labeled amount of levetiracetam. Inactive ingredients: colloidal silicon dioxide, croscarmellose sodium, magnesium stearate, polyethylene glycol 3350, polyethylene glycol 6000, polyvinyl alcohol, talc, titanium dioxide, and additional agents listed below:

250 mg tablets: FD&C Blue #2/indigo carmine aluminum lake
500 mg tablets: iron oxide yellow
750 mg tablets: FD&C yellow #6/sunset yellow FCF aluminum lake, iron oxide red

KEPPRA oral solution contains 100 mg of levetiracetam per mL. Inactive ingredients: ammonium glycyrrhizinate, citric acid monohydrate, glycerin, maltitol solution, methylparaben, potassium acesulfame, propylparaben, purified water, sodium citrate dihydrate and natural and artificial flavor.

12 CLINICAL PHARMACOLOGY

12.1 Mechanism Of Action

The precise mechanism(s) by which levetiracetam exerts its antiepileptic effect is unknown. The antiepileptic activity of levetiracetam was assessed in a number of animal models of epileptic seizures. Levetiracetam did not inhibit single seizures induced by maximal stimulation with electrical current or different chemoconvulsants and showed only minimal activity in submaximal stimulation and in threshold tests. Protection was observed, however, against secondarily generalized activity from focal seizures induced by pilocarpine and kainic acid, two chemoconvulsants that induce seizures that mimic some features of human complex partial seizures with secondary generalization. Levetiracetam also displayed inhibitory properties in the kindling model in rats, another model of human complex partial seizures, both during kindling development and in the fully kindled state. The predictive value of these animal models for specific types of human epilepsy is uncertain.

In vitro and in vivo recordings of epileptiform activity from the hippocampus have shown that levetiracetam inhibits burst firing without affecting normal neuronal excitability, suggesting that levetiracetam may selectively prevent hypersynchronization of epileptiform burst firing and propagation of seizure activity.

Levetiracetam at concentrations of up to 10 µM did not demonstrate binding affinity for a variety of known receptors, such as those associated with benzodiazepines, GABA (gamma-aminobutyric acid), glycine, NMDA (N-methyl-D-aspartate), re-uptake sites, and second messenger systems. Furthermore, in vitro studies have failed to find an effect of levetiracetam on neuronal voltage-gated sodium or T-type calcium currents and levetiracetam does not appear to directly facilitate GABAergic neurotransmission. However, in vitro studies have demonstrated that levetiracetam opposes the activity of negative modulators of GABA- and glycine-gated currents and partially inhibits N-type calcium currents in neuronal cells.

A saturable and stereoselective neuronal binding site in rat brain tissue has been described for levetiracetam. Experimental data indicate that this binding site is the synaptic vesicle protein SV2A, thought to be involved in the regulation of vesicle exocytosis. Although the molecular significance of levetiracetam binding to SV2A is not understood, levetiracetam and related analogs showed a rank order of affinity for SV2A which correlated with the potency of their antiseizure activity in audiogenic seizure-prone mice. These findings suggest that the interaction of levetiracetam with the SV2A protein may contribute to the antiepileptic mechanism of action of the drug.

12.2 Pharmacodynamics

Effects on QTc Interval

The effect of KEPPRA on QTc prolongation was evaluated in a randomized, double-blind, positive-controlled (moxifloxacin 400 mg)- and placebo-controlled crossover study of KEPPRA (1000 mg or 5000 mg) in 52 healthy subjects. The upper bound of the 90% confidence interval for the largest placebo-adjusted, baseline-corrected QTc was below 10 milliseconds. Therefore, there was no evidence of significant QTc prolongation in this study.

12.3 Pharmacokinetics

Absorption and Distribution

Absorption of levetiracetam is rapid, with peak plasma concentrations occurring in about an hour following oral administration in fasted subjects. The oral bioavailability of levetiracetam tablets is 100% and the tablets and oral solution are bioequivalent in rate and extent of absorption. Food does not affect the extent of absorption of levetiracetam but it decreases Cmax by 20% and delays Tmax by 1.5 hours. The pharmacokinetics of levetiracetam are linear over the dose range of 500-5000 mg. Steady state is achieved after 2 days of multiple twice-daily dosing. Levetiracetam and its major metabolite are less than 10% bound to plasma proteins; clinically significant interactions with other drugs through competition for protein binding sites are therefore unlikely.

Metabolism

Levetiracetam is not extensively metabolized in humans. The major metabolic pathway is the enzymatic hydrolysis of the acetamide group, which produces the carboxylic acid metabolite, ucb L057 (24% of dose) and is not dependent on any liver cytochrome P450 isoenzymes. The major metabolite is inactive in animal seizure models. Two minor metabolites were identified as the product of hydroxylation of the 2-oxo-pyrrolidine ring (2% of dose) and opening of the 2-oxo-pyrrolidine ring in position 5 (1% of dose). There is no enantiomeric interconversion of levetiracetam or its major metabolite.

Elimination

Levetiracetam plasma half-life in adults is 7 ± 1 hour and is unaffected by either dose or repeated administration. Levetiracetam is eliminated from the systemic circulation by renal excretion as unchanged drug which represents 66% of administered dose. The total body clearance is 0.96 mL/min/kg and the renal clearance is 0.6 mL/min/kg. The mechanism of excretion is glomerular filtration with subsequent partial tubular reabsorption. The metabolite ucb L057 is excreted by glomerular filtration and active tubular secretion with a renal clearance of 4 mL/min/kg. Levetiracetam elimination is correlated to creatinine clearance. Levetiracetam clearance is reduced in patients with impaired renal function [see Use in Specific Populations (8.6) and Dosage and Administration (2.5)].

Specific Populations:

Elderly

Pharmacokinetics of levetiracetam were evaluated in 16 elderly subjects (age 61-88 years) with creatinine clearance ranging from 30 to 74 mL/min. Following oral administration of twice-daily dosing for 10 days, total body clearance decreased by 38% and the half-life was 2.5 hours longer in the elderly compared to healthy adults. This is most likely due to the decrease in renal function in these subjects.

Pediatric Patients

Pharmacokinetics of levetiracetam were evaluated in 24 pediatric patients (age 6-12 years) after single dose (20 mg/kg). The body weight adjusted apparent clearance of levetiracetam was approximately 40% higher than in adults.

A repeat dose pharmacokinetic study was conducted in pediatric patients (age 4-12 years) at doses of 20 mg/kg/day, 40 mg/kg/day, and 60 mg/kg/day. The evaluation of the pharmacokinetic profile of levetiracetam and its metabolite (ucb L057) in 14 pediatric patients demonstrated rapid absorption of levetiracetam at all doses with a Tmax of about 1 hour and a t1/2 of 5 hours across the three dosing levels. The pharmacokinetics of levetiracetam in children was linear between 20 to 60 mg/kg/day. The potential interaction of levetiracetam with other AEDs was also evaluated in these patients. Levetiracetam had no significant effect on the plasma concentrations of carbamazepine, valproic acid, topiramate or lamotrigine. However, there was about a 22% increase of apparent clearance of levetiracetam when it was co-administered with an enzyme-inducing AED (e.g. carbamazepine).

Following single dose administration (20 mg/kg) of a 10% oral solution to children with epilepsy (1 month to < 4 years), levetiracetam was rapidly absorbed and peak plasma concentrations were observed approximately 1 hour after dosing. The pharmacokinetic results indicated that half-life was shorter (5.3 h) than for adults (7.2 h) and apparent clearance was faster (1.5 mL/min/kg) than for adults (0.96 mL/min/kg).

Population pharmacokinetic analysis showed that body weight was significantly correlated to the clearance of levetiracetam in pediatric patients; clearance increased with an increase in body weight.

Pregnancy

Keppra levels may decrease during pregnancy.

Gender

Levetiracetam Cmax and AUC were 20% higher in women (N=11) compared to men (N=12). However, clearances adjusted for body weight were comparable.

Race

Formal pharmacokinetic studies of the effects of race have not been conducted. Cross study comparisons involving Caucasians (N=12) and Asians (N=12), however, show that pharmacokinetics of levetiracetam were comparable between the two races. Because levetiracetam is primarily renally excreted and there are no important racial differences in creatinine clearance, pharmacokinetic differences due to race are not expected.

Renal Impairment

The disposition of levetiracetam was studied in adult subjects with varying degrees of renal function. Total body clearance of levetiracetam is reduced in patients with impaired renal function by 40% in the mild group (CLcr = 50-80 mL/min), 50% in the moderate group (CLcr = 30-50 mL/min) and 60% in the severe renal impairment group (CLcr <30 mL/min). Clearance of levetiracetam is correlated with creatinine clearance.

In anuric (end stage renal disease) patients, the total body clearance decreased 70% compared to normal subjects (CLcr >80 mL/min). Approximately 50% of the pool of levetiracetam in the body is removed during a standard 4- hour hemodialysis procedure.

Dosage should be reduced in patients with impaired renal function receiving levetiracetam, and supplemental doses should be given to patients after dialysis [see Dosage and Administration (2.5)].

Hepatic Impairment

In subjects with mild (Child-Pugh A) to moderate (Child-Pugh B) hepatic impairment, the pharmacokinetics of levetiracetam were unchanged. In patients with severe hepatic impairment (Child-Pugh C), total body clearance was 50% that of normal subjects, but decreased renal clearance accounted for most of the decrease. No dose adjustment is needed for patients with hepatic impairment.

Drug Interactions:

In vitro data on metabolic interactions indicate that levetiracetam is unlikely to produce, or be subject to, pharmacokinetic interactions. Levetiracetam and its major metabolite, at concentrations well above Cmax levels achieved within the therapeutic dose range, are neither inhibitors of, nor high affinity substrates for, human liver cytochrome P450 isoforms, epoxide hydrolase or UDP-glucuronidation enzymes. In addition, levetiracetam does not affect the in vitro glucuronidation of valproic acid.

Potential pharmacokinetic interactions of or with levetiracetam were assessed in clinical pharmacokinetic studies (phenytoin, valproate, warfarin, digoxin, oral contraceptive, probenecid) and through pharmacokinetic screening in the placebo-controlled clinical studies in epilepsy patients.

Phenytoin

KEPPRA (3000 mg daily) had no effect on the pharmacokinetic disposition of phenytoin in patients with refractory epilepsy. Pharmacokinetics of levetiracetam were also not affected by phenytoin.

Valproate

KEPPRA (1500 mg twice daily) did not alter the pharmacokinetics of valproate in healthy volunteers. Valproate 500 mg twice daily did not modify the rate or extent of levetiracetam absorption or its plasma clearance or urinary excretion. There also was no effect on exposure to and the excretion of the primary metabolite, ucb L057.

Other Antiepileptic Drugs

Potential drug interactions between KEPPRA and other AEDs (carbamazepine, gabapentin, lamotrigine, phenobarbital, phenytoin, primidone and valproate) were also assessed by evaluating the serum concentrations of levetiracetam and these AEDs during placebo-controlled clinical studies. These data indicate that levetiracetam does not influence the plasma concentration of other AEDs and that these AEDs do not influence the pharmacokinetics of levetiracetam.

Effect Of AEDs In Pediatric Patients

There was about a 22% increase of apparent total body clearance of levetiracetam when it was co-administered with enzyme-inducing AEDs. Dose adjustment is not recommended. Levetiracetam had no effect on plasma concentrations of carbamazepine, valproate, topiramate, or lamotrigine.

Oral Contraceptives

KEPPRA (500 mg twice daily) did not influence the pharmacokinetics of an oral contraceptive containing 0.03 mg ethinyl estradiol and 0.15 mg levonorgestrel, or of the luteinizing hormone and progesterone levels, indicating that impairment of contraceptive efficacy is unlikely. Coadministration of this oral contraceptive did not influence the pharmacokinetics of levetiracetam.

Digoxin

KEPPRA (1000 mg twice daily) did not influence the pharmacokinetics and pharmacodynamics (ECG) of digoxin given as a 0.25 mg dose every day. Coadministration of digoxin did not influence the pharmacokinetics of levetiracetam.

Warfarin

KEPPRA (1000 mg twice daily) did not influence the pharmacokinetics of R and S warfarin. Prothrombin time was not affected by levetiracetam. Coadministration of warfarin did not affect the pharmacokinetics of levetiracetam.

Probenecid

Probenecid, a renal tubular secretion blocking agent, administered at a dose of 500 mg four times a day, did not change the pharmacokinetics of levetiracetam 1000 mg twice daily. Cssmax of the metabolite, ucb L057, was approximately doubled in the presence of probenecid while the fraction of drug excreted unchanged in the urine remained the same. Renal clearance of ucb L057 in the presence of probenecid decreased 60%, probably related to competitive inhibition of tubular secretion of ucb L057. The effect of KEPPRA on probenecid was not studied.

13 NONCLINICAL TOXICOLOGY

13.1 Carcinogenesis, Mutagenesis, Impairment Of Fertility

Carcinogenesis

Rats were dosed with levetiracetam in the diet for 104 weeks at doses of 50, 300 and 1800 mg/kg/day. The highest dose is 6 times the maximum recommended daily human dose (MRHD) of 3000 mg on a mg/m^2 basis and it also provided systemic exposure (AUC) approximately 6 times that achieved in humans receiving the MRHD. There was no evidence of carcinogenicity. In mice, oral administration of levetiracetam for 80 weeks (doses up to 960 mg/kg/day) or 2 years (doses up to 4000 mg/kg/day, lowered to 3000 mg/kg/day after 45 weeks due to intolerablility) was not associated with an increase in tumors. The highest dose tested in mice for 2 years (3000 mg/kg/day) is approximately 5 times the MRHD on a mg/m^2 basis.

Mutagenesis

Levetiracetam was not mutagenic in the Ames test or in mammalian cells in vitro in the Chinese hamster ovary/HGPRT locus assay. It was not clastogenic in an in vitro analysis of metaphase chromosomes obtained from Chinese hamster ovary cells or in an in vivo mouse micronucleus assay. The hydrolysis product and major human metabolite of levetiracetam (ucb L057) was not mutagenic in the Ames test or the in vitro mouse lymphoma assay.

Impairment Of Fertility

No adverse effects on male or female fertility or reproductive performance were observed in rats at oral doses up to 1800 mg/kg/day (6 times the maximum recommended human dose on a mg/m^2 or systemic exposure [AUC] basis).

14 CLINICAL STUDIES

In the following studies, statistical significance versus placebo indicates a p value <0.05.

14.1 Partial Onset Seizures

Effectiveness In Partial Onset Seizures In Adults With Epilepsy

The effectiveness of KEPPRA as adjunctive therapy (added to other antiepileptic drugs) in adults was established in three multicenter, randomized, double-blind, placebo-controlled clinical studies in patients who had refractory partial onset seizures with or without secondary generalization. The tablet formulation was used in all these studies. In these studies, 904 patients were randomized to placebo, 1000 mg, 2000 mg, or 3000 mg/day. Patients enrolled in Study 1 or Study 2 had refractory partial onset seizures for at least two years and had taken two or more classical AEDs. Patients enrolled in Study 3 had refractory partial onset seizures for at least 1 year and had taken one classical AED. At the time of the study, patients were taking a stable dose regimen of at least one and could take a maximum of two AEDs. During the baseline period, patients had to have experienced at least two partial onset seizures during each 4-week period.

Study 1

Study 1 was a double-blind, placebo-controlled, parallel-group study conducted at 41 sites in the United States comparing KEPPRA 1000 mg/day (N=97), KEPPRA 3000 mg/day (N=101), and placebo (N=95) given in equally divided doses twice daily. After a prospective baseline period of 12 weeks, patients were randomized to one of the three treatment groups described above. The 18-week treatment period consisted of a 6-week titration period, followed by a 12-week fixed dose evaluation period, during which concomitant AED regimens were held constant. The primary measure of effectiveness was a between group comparison of the percent reduction in weekly partial seizure frequency relative to placebo over the entire randomized treatment period (titration + evaluation period). Secondary outcome variables included the responder rate (incidence of patients with ≥50% reduction from baseline in partial onset seizure frequency). The results of the analysis of Study 1 are displayed in Table 10.

Table 10: Reduction In Mean Over Placebo In Weekly Frequency Of Partial Onset Seizures In Study 1
 | Placebo (N=95) | KEPPRA 1000 mg/day (N=97) | KEPPRA 3000 mg/day (N=101)
Percent reduction in partial seizure frequency over placebo | – | 26.1% [statistically significant versus placebo] | 30.1%

The percentage of patients (y-axis) who achieved ≥50% reduction in weekly seizure rates from baseline in partial onset seizure frequency over the entire randomized treatment period (titration + evaluation period) within the three treatment groups (x-axis) is presented in Figure 1.

Figure 1: Responder Rate (≥50% Reduction From Baseline) In Study 1

*statistically significant versus placebo

Study 2

Study 2 was a double-blind, placebo-controlled, crossover study conducted at 62 centers in Europe comparing KEPPRA 1000 mg/day (N=106), KEPPRA 2000 mg/day (N=105), and placebo (N=111) given in equally divided doses twice daily.

The first period of the study (Period A) was designed to be analyzed as a parallel-group study. After a prospective baseline period of up to 12 weeks, patients were randomized to one of the three treatment groups described above. The 16-week treatment period consisted of the 4-week titration period followed by a 12-week fixed dose evaluation period, during which concomitant AED regimens were held constant. The primary measure of effectiveness was a between group comparison of the percent reduction in weekly partial seizure frequency relative to placebo over the entire randomized treatment period (titration + evaluation period). Secondary outcome variables included the responder rate (incidence of patients with ≥50% reduction from baseline in partial onset seizure frequency). The results of the analysis of Period A are displayed in Table 11.

Table 11: Reduction In Mean Over Placebo In Weekly Frequency Of Partial Onset Seizures In Study 2: Period A
 | Placebo (N=111) | KEPPRA 1000 mg/day (N=106) | KEPPRA 2000 mg/day (N=105)
Percent reduction in partial seizure frequency over placebo | – | 17.1% [statistically significant versus placebo] | 21.4%

The percentage of patients (y-axis) who achieved ≥50% reduction in weekly seizure rates from baseline in partial onset seizure frequency over the entire randomized treatment period (titration + evaluation period) within the three treatment groups (x-axis) is presented in Figure 2.

Figure 2: Responder Rate (≥50% Reduction From Baseline) In Study 2: Period A

*statistically significant versus placebo

The comparison of KEPPRA 2000 mg/day to KEPPRA 1000 mg/day for responder rate was statistically significant (P=0.02). Analysis of the trial as a cross-over yielded similar results.

Study 3

Study 3 was a double-blind, placebo-controlled, parallel-group study conducted at 47 centers in Europe comparing KEPPRA 3000 mg/day (N=180) and placebo (N=104) in patients with refractory partial onset seizures, with or without secondary generalization, receiving only one concomitant AED. Study drug was given in two divided doses. After a prospective baseline period of 12 weeks, patients were randomized to one of two treatment groups described above. The 16-week treatment period consisted of a 4-week titration period, followed by a 12-week fixed dose evaluation period, during which concomitant AED doses were held constant. The primary measure of effectiveness was a between group comparison of the percent reduction in weekly seizure frequency relative to placebo over the entire randomized treatment period (titration + evaluation period). Secondary outcome variables included the responder rate (incidence of patients with ≥50% reduction from baseline in partial onset seizure frequency). Table 12 displays the results of the analysis of Study 3.

Table 12: Reduction In Mean Over Placebo In Weekly Frequency Of Partial Onset Seizures In Study 3
 | Placebo (N=104) | KEPPRA 3000 mg/day (N=180)
Percent reduction in partial seizure frequency over placebo | – | 23.0% [statistically significant versus placebo]

The percentage of patients (y-axis) who achieved ≥50% reduction in weekly seizure rates from baseline in partial onset seizure frequency over the entire randomized treatment period (titration + evaluation period) within the two treatment groups (x-axis) is presented in Figure 3.

Figure 3: Responder Rate (≥50% Reduction From Baseline) In Study 3

*statistically significant versus placebo

Effectiveness In Partial Onset Seizures In Pediatric Patients 4 Years To 16 Years With Epilepsy

The effectiveness of KEPPRA as adjunctive therapy (added to other antiepileptic drugs) in pediatric patients was established in one multicenter, randomized double-blind, placebo-controlled study, conducted at 60 sites in North America, in children 4 to 16 years of age with partial seizures uncontrolled by standard antiepileptic drugs (AEDs). Eligible patients on a stable dose of 1-2 AEDs, who still experienced at least 4 partial onset seizures during the 4 weeks prior to screening, as well as at least 4 partial onset seizures in each of the two 4-week baseline periods, were randomized to receive either KEPPRA or placebo. The enrolled population included 198 patients (KEPPRA N=101, placebo N=97) with refractory partial onset seizures, whether or not secondarily generalized. The study consisted of an 8-week baseline period and 4-week titration period followed by a 10-week evaluation period. Dosing was initiated at a dose of 20 mg/kg/day in two divided doses. During the treatment period, KEPPRA doses were adjusted in 20 mg/kg/day increments, at 2-week intervals to the target dose of 60 mg/kg/day. The primary measure of effectiveness was a between group comparison of the percent reduction in weekly partial seizure frequency relative to placebo over the entire 14-week randomized treatment period (titration + evaluation period). Secondary outcome variables included the responder rate (incidence of patients with ≥ 50% reduction from baseline in partial onset seizure frequency per week). Table 13 displays the results of this study.

Table 13: Reduction In Mean Over Placebo In Weekly Frequency Of Partial Onset Seizures
 | Placebo (N=97) | KEPPRA (N=101)
Percent reduction in partial seizure frequency over placebo | - | 26.8% [statistically significant versus placebo]

The percentage of patients (y-axis) who achieved ≥ 50% reduction in weekly seizure rates from baseline in partial onset seizure frequency over the entire randomized treatment period (titration + evaluation period) within the two treatment groups (x-axis) is presented in Figure 4.

Figure 4: Responder Rate (≥ 50% Reduction From Baseline)

*statistically significant versus placebo

Effectiveness In Partial Onset Seizures In Pediatric Patients 1 Month To <4 Years With Epilepsy

The effectiveness of KEPPRA as adjunctive therapy in pediatric patients was established in one multicenter, randomized double-blind, placebo-controlled study, conducted at 62 sites in North America, South America, and Europe in children 1 month to less than 4 years of age with partial seizures, uncontrolled by standard epileptic drugs (AEDs). Eligible patients on a stable dose of 1-2 AEDs, who experienced at least 2 partial onset seizures during the 48-hour baseline video EEG were randomized to receive either KEPPRA or placebo. The enrolled population included 116 patients (KEPPRA N=60, placebo N=56) with refractory partial onset seizures, whether or not secondarily generalized. Randomization was stratified by age range as follows: 1 month to less than 6 months of age (N=4 treated with KEPPRA), 6 months to less than 1 year of age (N=8 treated with KEPPRA), 1 year to less than 2 years of age (N=20 treated with KEPPRA), and 2 years to less than 4 years of age (N=28 treated with KEPPRA). The study consisted of a 5-day evaluation period which included a 1-day titration period followed by a 4-day maintenance period. KEPPRA dosing was determined by age and weight as follows: children 1 month to less than 6 months old were randomized to a target dose of 40 mg/kg/day, and children 6 months to less than 4 years old were randomized to a target dose of 50 mg/kg/day. The primary measure of effectiveness was the responder rate (percent of patients with ≥ 50% reduction from baseline in average daily partial onset seizure frequency) assessed by a blinded central reader using a 48-hour video EEG performed during the last two days of the 4-day maintenance period. A total of 109 patients were included in the efficacy analysis. A statistically significant difference between KEPPRA and placebo was observed (see Figure 5). The treatment effect associated with KEPPRA was consistent across age groups.

Figure 5: Responder Rate For All Subjects Ages 1 Month to < 4 Years (≥ 50% Reduction From Baseline)

*Statistically significant versus placebo

14.2 Myoclonic Seizures In Patients With Juvenile Myoclonic Epilepsy

Effectiveness Of Myoclonic Seizures In Patients ≥12 Years Of Age With Juvenile Myoclonic Epilepsy (JME)

The effectiveness of KEPPRA as adjunctive therapy (added to other antiepileptic drugs) in patients 12 years of age and older with juvenile myoclonic epilepsy (JME) experiencing myoclonic seizures was established in one multicenter, randomized, double-blind, placebo-controlled study, conducted at 37 sites in 14 countries. Of the 120 patients enrolled, 113 had a diagnosis of confirmed or suspected JME. Eligible patients on a stable dose of 1 antiepileptic drug (AED) experiencing one or more myoclonic seizures per day for at least 8 days during the prospective 8-week baseline period were randomized to either KEPPRA or placebo (KEPPRA N=60, placebo N=60). Patients were titrated over 4 weeks to a target dose of 3000 mg/day and treated at a stable dose of 3000 mg/day over 12 weeks (evaluation period). Study drug was given in 2 divided doses.

The primary measure of effectiveness was the proportion of patients with at least 50% reduction in the number of days per week with one or more myoclonic seizures during the treatment period (titration + evaluation periods) as compared to baseline. Table 14 displays the results for the 113 patients with JME in this study.

Table 14: Responder Rate (≥50% Reduction From Baseline) In Myoclonic Seizure Days Per Week for Patients with JME
 | Placebo (N=59) | KEPPRA (N=54)
Percentage of responders | 23.7% | 60.4% [statistically significant versus placebo]

14.3 Primary Generalized Tonic-Clonic Seizures

Effectiveness In Primary Generalized Tonic-Clonic Seizures In Patients ≥6 Years Of Age

The effectiveness of KEPPRA as adjunctive therapy (added to other antiepileptic drugs) in patients 6 years of age and older with idiopathic generalized epilepsy experiencing primary generalized tonic-clonic (PGTC) seizures was established in one multicenter, randomized, double-blind, placebo-controlled study, conducted at 50 sites in 8 countries. Eligible patients on a stable dose of 1 or 2 antiepileptic drugs (AEDs) experiencing at least 3 PGTC seizures during the 8-week combined baseline period (at least one PGTC seizure during the 4 weeks prior to the prospective baseline period and at least one PGTC seizure during the 4-week prospective baseline period) were randomized to either KEPPRA or placebo. The 8-week combined baseline period is referred to as "baseline" in the remainder of this section. The population included 164 patients (KEPPRA N=80, placebo N=84) with idiopathic generalized epilepsy (predominately juvenile myoclonic epilepsy, juvenile absence epilepsy, childhood absence epilepsy, or epilepsy with Grand Mal seizures on awakening) experiencing primary generalized tonic-clonic seizures. Each of these syndromes of idiopathic generalized epilepsy was well represented in this patient population. Patients were titrated over 4 weeks to a target dose of 3000 mg/day for adults or a pediatric target dose of 60 mg/kg/day and treated at a stable dose of 3000 mg/day (or 60 mg/kg/day for children) over 20 weeks (evaluation period). Study drug was given in 2 equally divided doses per day.

The primary measure of effectiveness was the percent reduction from baseline in weekly PGTC seizure frequency for KEPPRA and placebo treatment groups over the treatment period (titration + evaluation periods). There was a statistically significant decrease from baseline in PGTC frequency in the KEPPRA-treated patients compared to the placebo-treated patients.

Table 15: Median Percent Reduction From Baseline In PGTC Seizure Frequency Per Week
 | Placebo (N=84) | KEPPRA (N=78)
Percent reduction in PGTC seizure frequency | 44.6% | 77.6% [statistically significant versus placebo]

The percentage of patients (y-axis) who achieved ≥50% reduction in weekly seizure rates from baseline in PGTC seizure frequency over the entire randomized treatment period (titration + evaluation period) within the two treatment groups (x-axis) is presented in Figure 6.

Figure 6: Responder Rate (≥50% Reduction From Baseline) In PGTC Seizure Frequency Per Week

*statistically significant versus placebo

16 HOW SUPPLIED/STORAGE AND HANDLING

16.1 How Supplied

KEPPRA 500 mg tablets are yellow, oblong-shaped, scored, film-coated tablets debossed with "ucb 500" on one side. They are supplied in white HDPE bottles containing 30 tablets (NDC 54868-4947-0); bottles containing 60 tablets (NDC 54868-4947-2); and bottles containing 90 tablets (NDC 54868-4947-1).

KEPPRA 750 mg tablets are orange, oblong-shaped, scored, film-coated tablets debossed with "ucb 750" on one side. They are supplied in white HDPE bottles containing 30 tablets (NDC 54868-5266-1); and bottles containing 60 tablets (NDC 54868-5266-0).

16.2 Storage

Store at 25°C (77°F); excursions permitted to 15 to 30°C (59 to 86°F) [see USP Controlled Room Temperature].

17 PATIENT COUNSELING INFORMATION

See FDA-approved Patient Labeling (Medication Guide).

Counsel patients on the benefits and risks of receiving KEPPRA. Provide the Medication Guide to patients and/or caregivers, and instruct them to read the Medication Guide prior to taking KEPPRA. Instruct patients to take KEPPRA only as prescribed.

Suicidal Behavior and Ideation

Counsel patients, their caregivers, and/or families that antiepileptic drugs (AEDs), including KEPPRA, may increase the risk of suicidal thoughts and behavior and advise patients to be alert for the emergence or worsening of symptoms of depression; unusual changes in mood or behavior; or suicidal thoughts, behavior, or thoughts about self-harm. Advise patients, their caregivers, and/or families to immediately report behaviors of concern to a healthcare provider.

Psychiatric Reactions and Changes in Behavior

Advise patients that KEPPRA may cause changes in behavior (e.g. aggression, agitation, anger, anxiety, apathy, depression, hostility, and irritability) and in rare cases, psychotic symptoms have occurred.

Effects on Driving or Operating Machinery

Inform patients that KEPPRA may cause dizziness and somnolence. Inform patients not to drive or operate machinery until they have gained sufficient experience on KEPPRA to gauge whether it adversely affects their ability to drive or operate machinery.

Dermatological Adverse Reactions

Advise patients that serious dermatological adverse reactions have occurred in patients treated with KEPPRA and instruct them to call their physician immediately if a rash develops.

Pregnancy

Advise patients to notify their healthcare provider if they become pregnant or intend to become pregnant during KEPPRA therapy. Encourage patients to enroll in the North American Antiepileptic Drug (NAAED) pregnancy registry if they become pregnant. This registry is collecting information about the safety of antiepileptic drugs during pregnancy. To enroll, patients can call the toll free number 1-888-233-2334. Additionally, inform patients they can enroll in the UCB AED Pregnancy Registry and they or their healthcare provider can call 1-888-537-7734 (toll free) [see Use In Specific Populations (8.1)].

KEPPRA Tablets and KEPPRA Oral Solution manufactured for
UCB, Inc.
Smyrna, GA 30080

KEPPRA is a registered trademark of the UCB Group of companies
© 2011, UCB, Inc., Smyrna, GA 30080
All rights reserved.
Printed in the U.S.A.

Relabeling and Repackaging by:
Physicians Total Care, Inc.
Tulsa, Oklahoma 74146

MEDICATION GUIDE

KEPPRA® (KEPP-ruh) (levetiracetam)
tablets and oral solution

Read this Medication Guide before you start taking KEPPRA and each time you get a refill. There may be new information. This information does not take the place of talking to your healthcare provider about your medical condition or treatment.

What is the most important information I should know about KEPPRA?

Like other antiepileptic drugs, KEPPRA may cause suicidal thoughts or actions in a very small number of people, about 1 in 500 people taking it.

Call a healthcare provider right away if you have any of these symptoms, especially if they are new, worse, or worry you:

- thoughts about suicide or dying
- attempts to commit suicide
- new or worse depression
- new or worse anxiety
- feeling agitated or restless
- panic attacks
- trouble sleeping (insomnia)
- new or worse irritability
- acting aggressive, being angry, or violent
- acting on dangerous impulses
- an extreme increase in activity and talking (mania)
- other unusual changes in behavior or mood

Do not stop KEPPRA without first talking to a healthcare provider.

- Stopping KEPPRA suddenly can cause serious problems. Stopping a seizure medicine suddenly can cause seizures that will not stop (status epilepticus).
- Suicidal thoughts or actions can be caused by things other than medicines. If you have suicidal thoughts or actions, your healthcare provider may check for other causes.

How can I watch for early symptoms of suicidal thoughts and actions?

- Pay attention to any changes, especially sudden changes, in mood, behaviors, thoughts, or feelings.
- Keep all follow-up visits with your healthcare provider as scheduled.
- Call your healthcare provider between visits as needed, especially if you are worried about symptoms.

What is KEPPRA?

KEPPRA is a prescription medicine taken by mouth that is used with other medicines to treat:

- partial onset seizures in people 1 month of age and older with epilepsy
- myoclonic seizures in people 12 years of age and older with juvenile myoclonic epilepsy
- primary generalized tonic-clonic seizures in people 6 years of age and older with certain types of generalized epilepsy.

It is not known if KEPPRA is safe or effective in children under 1 month of age.

Before taking your medicine, make sure you have received the correct medicine. Compare the name above with the name on your bottle and the appearance of your medicine with the description of KEPPRA provided below. Tell your pharmacist immediately if you think you have been given the wrong medicine.

250 mg KEPPRA tablets are blue, oblong-shaped, scored, film-coated tablets marked with "ucb 250" on one side.
500 mg KEPPRA tablets are yellow, oblong-shaped, scored, film-coated tablets marked with "ucb 500" on one side.
750 mg KEPPRA tablets are orange, oblong-shaped, scored, film-coated tablets marked with "ucb 750" on one side.
1000 mg KEPPRA tablets are white, oblong-shaped, scored, film-coated tablets marked with "ucb 1000" on one side.
KEPPRA oral solution is a clear, colorless, grape-flavored liquid.

What should I tell my healthcare provider before starting KEPPRA?

Before taking KEPPRA, tell your healthcare provider about all of your medical conditions, including if you:

- have or have had depression, mood problems or suicidal thoughts or behavior
- have kidney problems
- are pregnant or planning to become pregnant. It is not known if KEPPRA will harm your unborn baby. You and your healthcare provider will have to decide if you should take KEPPRA while you are pregnant. If you become pregnant while taking KEPPRA, talk to your healthcare provider about registering with the North American Antiepileptic Drug Pregnancy Registry. You can enroll in this registry by calling 1-888-233-2334. You can also enroll in the UCB AED Pregnancy Registry by calling 1-888-537-7734. The purpose of these registries is to collect information about the safety of KEPPRA and other antiepileptic medicine during pregnancy.
- are breast feeding. KEPPRA can pass into your milk and may harm your baby. You and your healthcare provider should discuss whether you should take KEPPRA or breast-feed; you should not do both.

Tell your healthcare provider about all the medicines you take, including prescription and nonprescription medicines, vitamins, and herbal supplements. Do not start a new medicine without first talking with your healthcare provider.

Know the medicines you take. Keep a list of them to show your healthcare provider and pharmacist each time you get a new medicine.

How should I take KEPPRA?

Take KEPPRA exactly as prescribed.

- Your healthcare provider will tell you how much KEPPRA to take and when to take it. KEPPRA is usually taken twice a day. Take KEPPRA at the same times each day.
- Your healthcare provider may change your dose. Do not change your dose without talking to your healthcare provider.
- Take KEPPRA with or without food.
- Swallow the tablets whole. Do not chew or crush tablets. Ask your healthcare provider for KEPPRA oral solution if you cannot swallow tablets.
- If your healthcare provider has prescribed KEPPRA oral solution, be sure to ask your pharmacist for a medicine dropper or medicine cup to help you measure the correct amount of KEPPRA oral solution. Do not use a household teaspoon. Ask your pharmacist for instructions on how to use the measuring device the right way.
- If you miss a dose of KEPPRA, take it as soon as you remember. If it is almost time for your next dose, just skip the missed dose. Take the next dose at your regular time. Do not take two doses at the same time.
- If you take too much KEPPRA, call your local Poison Control Center or go to the nearest emergency room right away.

What should I avoid while taking KEPPRA?

Do not drive, operate machinery or do other dangerous activities until you know how KEPPRA affects you. KEPPRA may make you dizzy or sleepy.

What are the possible side effects of KEPPRA?

- See "What is the most important information I should know about KEPPRA?"

KEPPRA can cause serious side effects.

Call your healthcare provider right away if you have any of these symptoms:

- mood and behavior changes such as aggression, agitation, anger, anxiety, apathy, mood swings, depression, hostility, and irritability. A few people may get psychotic symptoms such as hallucinations (seeing or hearing things that are really not there), delusions (false or strange thoughts or beliefs) and unusual behavior.
- extreme sleepiness, tiredness, and weakness
- problems with muscle coordination (problems walking and moving)
- a skin rash. Serious skin rashes can happen after you start taking KEPPRA. There is no way to tell if a mild rash will become a serious reaction.

The most common side effects seen in people who take KEPPRA include:

- sleepiness
- weakness
- infection
- dizziness

The most common side effects seen in children who take KEPPRA include, in addition to those listed above:

- tiredness
- acting aggressive
- nasal congestion
- decreased appetite
- irritability

These side effects can happen at any time but happen more often within the first 4 weeks of treatment except for infection.

Tell your healthcare provider if you have any side effect that bothers you or that does not go away.

These are not all the possible side effects of KEPPRA. For more information, ask your healthcare provider or pharmacist.

Call your doctor for medical advice about side effects. You may report side effects to FDA at 1-800-FDA-1088.

How should I store KEPPRA?

- Store KEPPRA at room temperature, 59°F to 86°F (15°C to 30°C) away from heat and light.
- Keep KEPPRA and all medicines out of the reach of children.

General information about KEPPRA.

Medicines are sometimes prescribed for purposes other than those listed in a Medication Guide. Do not use KEPPRA for a condition for which it was not prescribed. Do not give KEPPRA to other people, even if they have the same symptoms that you have. It may harm them.

This Medication Guide summarizes the most important information about KEPPRA. If you would like more information, talk with your healthcare provider. You can ask your pharmacist or healthcare provider for information about KEPPRA that is written for health professionals. You can also get information about KEPPRA at www.keppra.com or call 1-866-822-0068.

What are the ingredients of KEPPRA?

KEPPRA tablet active ingredient: levetiracetam
Inactive ingredients: colloidal silicon dioxide, croscarmellose sodium, magnesium stearate, polyethylene glycol 3350, polyethylene glycol 6000, polyvinyl alcohol, talc, titanium dioxide, and additional agents listed below:

250 mg tablets: FD&C Blue #2/indigo carmine aluminum lake
500 mg tablets: iron oxide yellow
750 mg tablets: FD&C yellow #6/sunset yellow FCF aluminum lake, iron oxide red

KEPPRA oral solution active ingredient: levetiracetam
Inactive ingredients: ammonium glycyrrhizinate, citric acid monohydrate, glycerin, maltitol solution, methylparaben, potassium acesulfame, propylparaben, purified water, sodium citrate dihydrate and natural and artificial flavor.

KEPPRA does not contain lactose or gluten. KEPPRA oral solution does contain carbohydrates. The liquid is dye-free.

This Medication Guide has been approved by the US Food and Drug Administration.

Distributed by
UCB, Inc.
Smyrna, GA 30080

KEPPRA is a registered trademark of the UCB Group of companies
© 2011, UCB, Inc., Smyrna, GA 30080
All rights reserved.
Printed in the U.S.A.

Rev. 12/2011

PRINCIPAL DISPLAY PANEL - 500 mg Tablet Bottle

Keppra®
(levetiracetam)

500 mg tablets

Dispense accompanying
Medication Guide to
each patient.

Rx only

PRINCIPAL DISPLAY PANEL - 750 mg Tablet Bottle

Keppra®
(levetiracetam)

750 mg tablets

Dispense accompanying
Medication Guide to
each patient.

Rx only